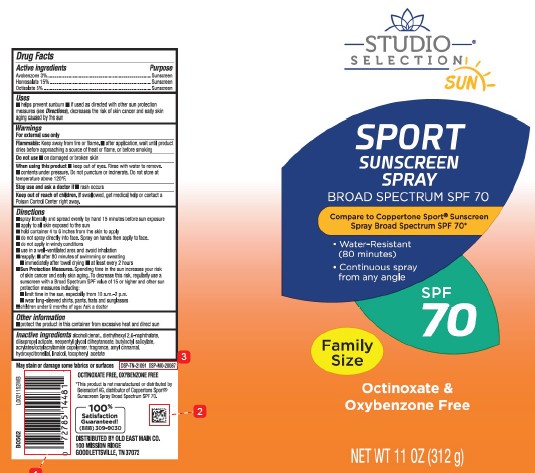 DRUG LABEL: Avobenzone, Homosalate, Octisalate
NDC: 75712-946 | Form: SPRAY
Manufacturer: Old East Main Co.
Category: otc | Type: HUMAN OTC DRUG LABEL
Date: 20260114

ACTIVE INGREDIENTS: AVOBENZONE 30 mg/1 g; HOMOSALATE 150 mg/1 g; OCTISALATE 50 mg/1 g
INACTIVE INGREDIENTS: ALCOHOL; DIETHYLHEXYL 2,6-NAPHTHALATE; DIISOPROPYL ADIPATE; NEOPENTYL GLYCOL DIHEPTANOATE; BUTYLOCTYL SALICYLATE; ACRYLATE/ISOBUTYL METHACRYLATE/N-TERT-OCTYLACRYLAMIDE COPOLYMER (40000 MW); .ALPHA.-AMYLCINNAMALDEHYDE; HYDROXYCITRONELLAL; LINALOOL, (+/-)-; .ALPHA.-TOCOPHEROL ACETATE

Studio Selection D46.000/D46AA
Sport Sunscreen Spray SPF 70

Active Ingredients

Avobenzone 3%

Homosalate 15%

Octisalate 5%

Purpose

Sunscreen

Uses

- helps prevent sunburn
- if used as directed with other sun protection measures (see Directions), decreases the risk of skin cancer and early skin aging caused by the sun

Warnings

For external use only

Flammable

Flammable:keep away from fire or flame.

- after application, wait until product dries before approaching a source of heat or flame, or before smoking

Do not use

on damaged or broken skin

When using this product

- keep out of eyes. Rinse with water to remove.
- contents under pressure. Do not puncture or incinerate. Do not store at temperature above 120°F.

Stop use and ask a doctor if

rash occurs

Keep out of reach of children.

If swallowed, get medical help or contact a Poison Control Center right away.

Directions

- spray liberally and spread evenly by hand 15 minutes before sun exposure
- apply to all skin exposed to the sun
- hold container 4 to 6 inches from the skin to apply
- do not spray directly into face. Spray on hands then apply to face.
- do not apply in windy conditions
- use in a well-ventilated area and avoid inhalation
- reapply:
- after 80 minutes of swimming or sweating
- immediately after towel drying
- at least every 2 hours
- Sun Protection Measures. Spending time in the sun increases your risk of skin cancer and early skin aging. To decrease this risk, regularly use a sunscreen with a Broad Spectrum SPF value of 15 or higher and other sun protection measures including:
- limit time in the sun, especially from 10 a.m.–2 p.m.
- wear long-sleeved shirts, pants, hats and sunglasses
- children under 6 months of age: Ask a doctor

Other information

protect the product in this container from excessive heat and direct sun

Inactive ingredients

alcohol denat., diethylhexyl 2,6-naphthalate, diisopropyl adipate, neopentyl glycol diheptanoate, butyloctyl salicylate, acrylates/octylacrylamide copolymer, fragrance, amyl cinnamal, hydroxycitronellal, linalool, tocopheryl acetate

Disclaimers

May stain or damage some fabrics or surfaces

OXTINOXATE FREE, OXYBENZONE FREE

*This product is not manufactured or distributed by Beiersdorf AG, distributor of Coppertone Sport® Sunscreen Spray Broad Spectrum SPF 70.

Adverse Reaction

DSP-TN-21091 DSP-MO-20087

DISTRIBUTED BY OLD EAST MAIN CO.

100 MISSION RIDGE

GOODLETSVILLE, TN 37072

100% Satisfaction Guaranteed!

(888) 309-9030

Principal display panel

STUDIO SELECTION®

SUN

SPORT

SUNSCREEN SPRAY

BROAD SPECTRUM SPF 70

Compare to Coppertone Sport®Broad Spectrum SPF 70*

- Water-Resistant (80 minutes)
- Continuous spray from any angle

SPF 70

Family Size

Octinoxate & Oxybenzone Free

NET WT 11 OZ (312 g)